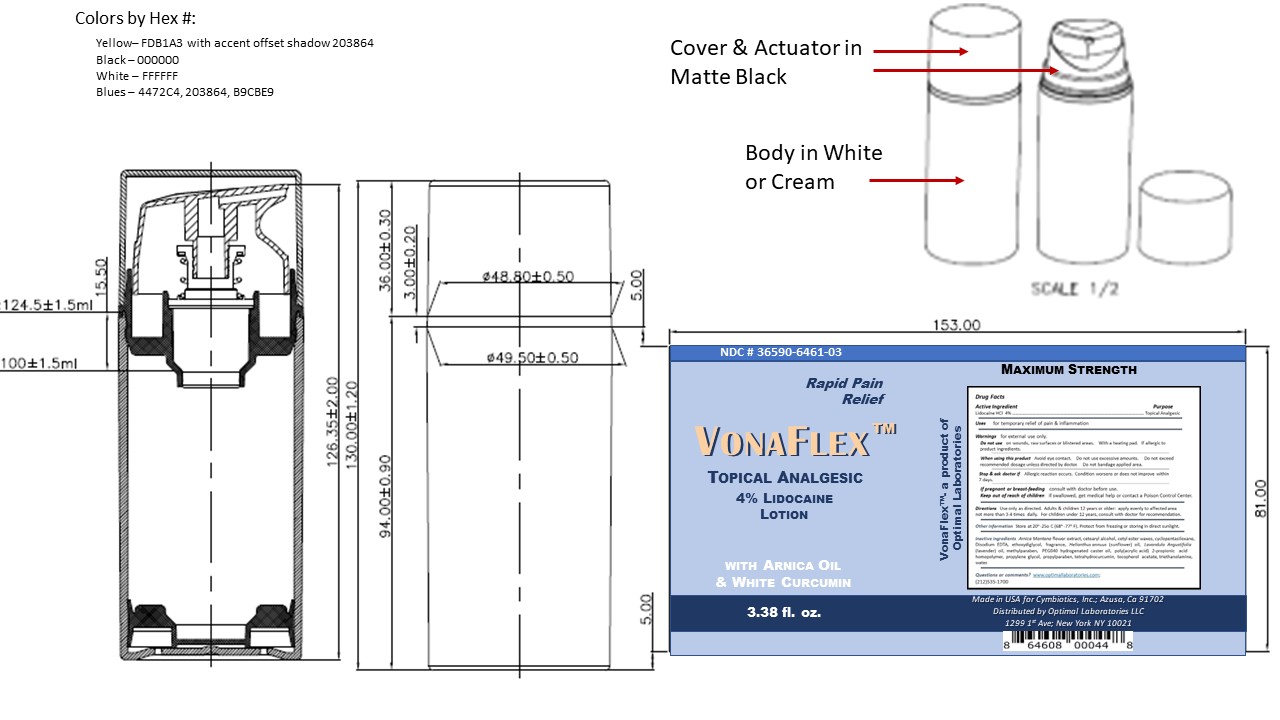 DRUG LABEL: Vonaflex
NDC: 36590-6461 | Form: LOTION
Manufacturer: Cymbiotics, Inc
Category: otc | Type: HUMAN OTC DRUG LABEL
Date: 20241213

ACTIVE INGREDIENTS: LIDOCAINE 4 g/100 g
INACTIVE INGREDIENTS: METHYLPARABEN 0.2 g/100 g; EDETATE DISODIUM 0.1 g/100 g; PROPYLPARABEN 0.02 g/100 g; WATER 71.93 g/100 g; SUNFLOWER OIL 0.75 g/100 g; CARBOMER 940 0.55 g/100 g; LAVENDER OIL 1 g/100 g; POLYOXYL 40 HYDROGENATED CASTOR OIL 1 g/100 g; PROPYLENE GLYCOL 4 g/100 g; DIETHYLENE GLYCOL MONOETHYL ETHER 5 g/100 g; CETYL ESTERS WAX 4 g/100 g; CETOSTEARYL ALCOHOL 2 g/100 g; TETRAHYDRODIFERULOYLMETHANE 2 g/100 g; TROLAMINE 1.5 g/100 g; .ALPHA.-TOCOPHEROL ACETATE 1.2 g/100 g; CYCLOMETHICONE 5 0.4 g/100 g; FRAGRANCE LAVENDER ROSE ORC1004596 0.1 g/100 g; ARNICA MONTANA FLOWER WATER 0.25 g/100 g

CY15-Vonaflex

Active Ingredient

Lidocaine 4%

Uses

For temporary relief of pain & inflammation

Uses

for temporary relief of pain & inflammation

Directions

Use only as directed. Adults & children 12 years or older: apply evenly to affected area not more than 3-4 x daily. For children under 12 years, consult with doctor for recommendations.

Change in heading as requested after review of draft

The Indications and Directions section was renameded to Dosage and Administration. This was noted as required 34068-7 This change was made on 7/21/2022 as directed.

07/26/22-- As per validation request, changed Directions to come under Dosage and Administration.

WARNINGS

For External use only.

Do not use:on wounds, raw surfaces or blistered areas, with a heating pad, or if allergic to product ingredients

When using this product:Avoid eye contact; do not use excessive amounts; do not exceed recommended dosage unless directed by doctor; do not bandage applied area.

Stop and ask doctor if:an allergic reaction occurs; condition worsens or does not improve within 7 days.

If pregnant or breast-feeding:consult with doctor before use.

if swallowed, get medical help or contact a Poison Control Center.

Precautions Concerning Children

Keep out of reach of children.

Other Information:

Store at 20o- 25oC (68o- 77oF),. Protect from freezing or storing in direct sunlight.

INACTIVE INGREDIENT

Arnica Montanaflower extract, cetearyl alcohol, cetyl ester waxes, cyclopentasiloxane, disodium EDTA, ethoxydiglycol, fragrance, Helianthus annuus(sunflower) oil, Lavandula Angustifolio(lavender) oil, methylparaben, PEG40 hydrogenated caster oil, poly(acrylic acid) 2-propionic acid homopolymer, propylene glycol, propylparaben, tetrahydrocurcumin, tocopherol acetate, triethanolamine, water.

Questions and Comments

www.optimallabortories.com

(212) 535-1700

Package Label and Principal Display Panel Vonaflex

NDC 36590-6451-03 front & back label